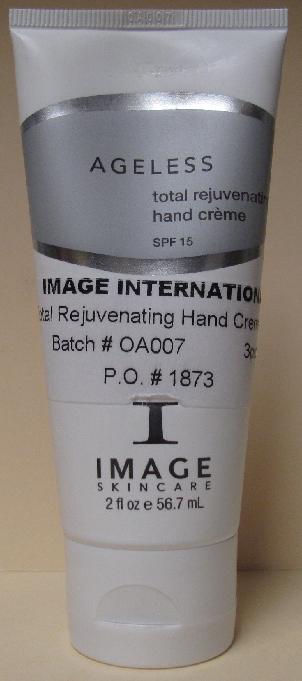 DRUG LABEL: AGELESS Total Rejuvenating Hand 
NDC: 62742-4036 | Form: CREAM
Manufacturer: Allure Labs, Inc.
Category: otc | Type: HUMAN OTC DRUG LABEL
Date: 20100701

ACTIVE INGREDIENTS: OCTINOXATE 75 mg/1 mL; OCTISALATE 50 mg/1 mL; AVOBENZONE 20 mg/1 mL; OCTOCRYLENE 20 mg/1 mL

Drug Facts

Active Ingredients:

1. Octinoxate (Ethylhexyl Methoxycinnamate) 7.5%

2. Octisalate (Ethylhexyl Salicylate) 5.0%

3. Butyl Methoxydibenzoylmethane (Parsol 1789, Avobenzone) 2.0%

4. Octocrylene 2.0%

Inactive Ingredients:

Water (Aqua), Caprylic/Capric Triglyceride (and) Linoleic acid (and) Glycine soja (Soybean) sterols (and) phospholepids, Caprylic/Capric Triglyceride (and) Diacetyl Boldine (Lumiskin), Kojic acid, Glycyrrhiza glabba (Licorice) root extract, Ubiquinone (Coenzyme Q10), Olea europea (Olive) leaf extract, Mushroom extract (Tricholoma matsutake singer)-enzyme-alcohol, Archtostaphylos uva ursi (Bearberry) leaf extract, Morus alba (Mulberry) leaf extract, Saccharomyces/Xylinum Black Tea Ferment-Glycerin-Hydroxyethylcellulose (Kombuchka), Dimethicone, Brassica compestris / Aleuritis fordi oil copolymer, Sodium Hyaluronate Crosspolymer, Phenoxyethanol and Caprylyl Glycol and Ethylhexyl Glycerin and Hexylene Glycol, Hydrolyzed Wheat Protein and Hydrolyzed Wheat Starch, Limnanthes alba (Meadowfoam) seed oil, PEG-60 Maracuja glycerides, Biosaccharide Gum-1, Portulac oleracea extract, Xanthan gum, Tetrahexyldecyl Ascorbate, Disodium EDTA.

Other information on back of the tube:

(Claims)

A Daily, super hydrating UVA/UVB broad spectrum moisturizer for the hands. Diminishes age spots with a blend of natural skin lightening agents, protects against harmful effects of the sun and builds up collagen to restore youthful skin. Contains eoenzyme Q10 and other anti-oxidants to fight against free radicals and environmental danmage.

Indications:

Signs of aging skin, age spots, dry, dehydrated skin.

Directions:

Apply daily for maximum protection and moisture. Reapply throughout the day and while exposed to the sun.

Reapply while exposed to Sun.

Distributor:

Image International

Palm Beach, FL 33411 USA

Image of the Product:

AGELESS Total Rejuvenating Hand Creme